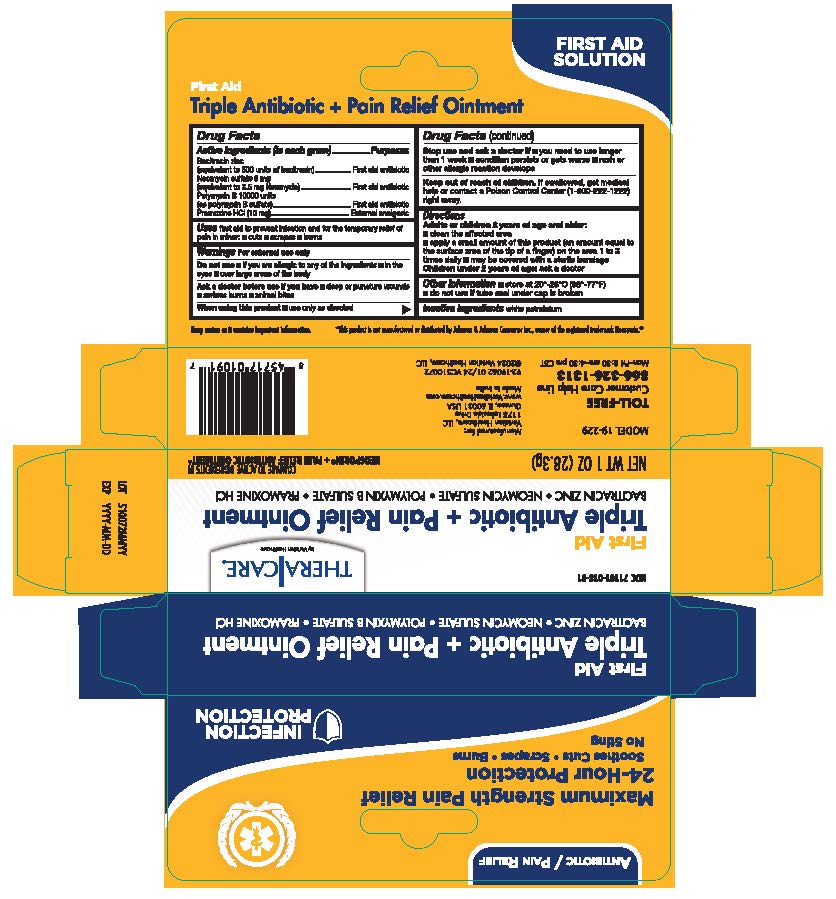 DRUG LABEL: TheraCare Triple Antibiotic
NDC: 71101-018 | Form: OINTMENT
Manufacturer: Veridian Healthcare
Category: otc | Type: HUMAN OTC DRUG LABEL
Date: 20260129

ACTIVE INGREDIENTS: BACITRACIN ZINC 400 [iU]/1 g; NEOMYCIN SULFATE 3.5 mg/1 g; POLYMYXIN B SULFATE 5000 [iU]/1 g; PRAMOXINE HCL 10 mg/1 g
INACTIVE INGREDIENTS: WHITE PETROLATUM

TheraCare Triple Antibiotic Ointment plus Pain relief

Active Ingredients

- Bacitracin zinc
- Neomycin sulfate
- Polymyxin B Sulfate
- Pramoxine HCL

PURPOSE

First aid antibiotic

External analgesic

Use

first aid to help prevent infection in minor:

- cuts
- scrapes
- burns

Warnings

For external use only.

Do not use

- if you are allergic to any of the ingredients
- in the eyes
- over large areas of the body

Ask a doctor before use if you have

- deep or puncture wounds
- animal bites
- serious burns

When Using this product

use only as directed

Stop use and ask a doctor if

- you need to use longer than 1 week
- condition persists or gets worse
- rash or other allergic reaction develops

Keep out of reach of children.If swallowed, get medical help or contact a Poison Control Center right away.(1-800-222-1222)

Directions

- Adults or children 2 years of age and older:
  ■clean the affected area
  ■apply a small amount of this product (an amount equal to the surface area of the tip of a finger) on the area 1 to 3 times daily
- ■may be covered w th a sterile bandage
- Children under 2 years of age: ask a doctor

Other information

- store at 20° to 25°C (68° to 77° F)
- do not use if tube seal under cap is broken

Inactive ingredients

white petrolatum